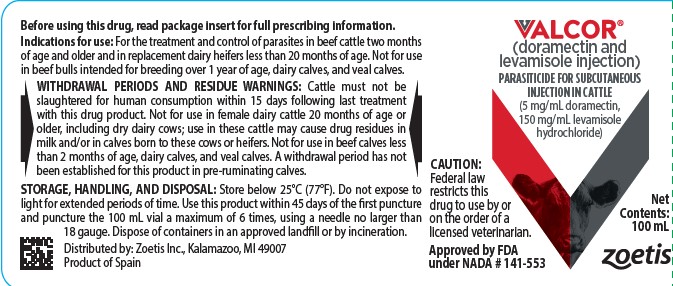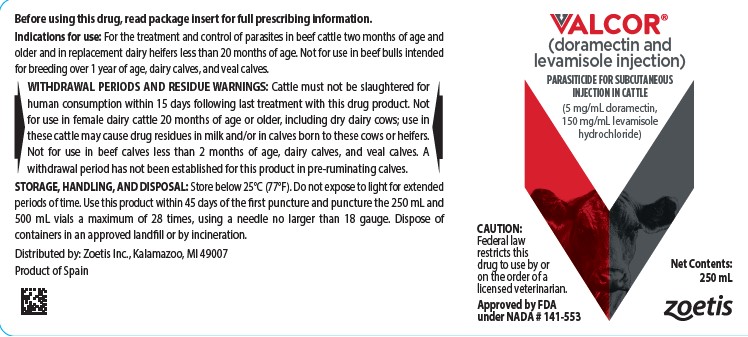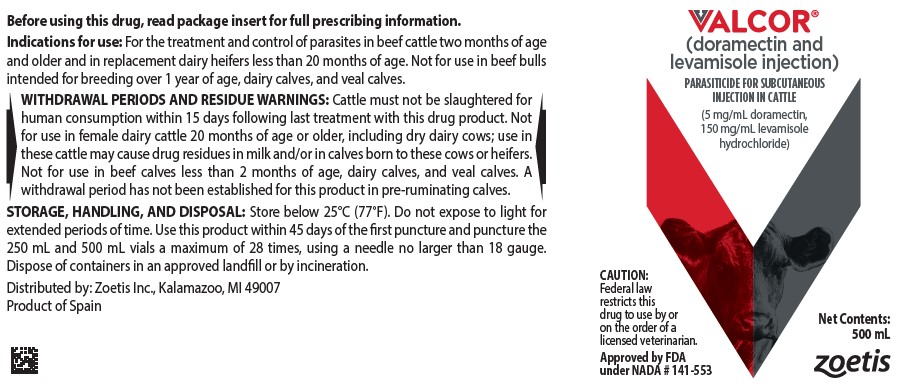 DRUG LABEL: Valcor
NDC: 54771-1685 | Form: INJECTION, SOLUTION
Manufacturer: Zoetis Inc.
Category: animal | Type: PRESCRIPTION ANIMAL DRUG LABEL
Date: 20250813

ACTIVE INGREDIENTS: DORAMECTIN 5 mg/1 mL; LEVAMISOLE HYDROCHLORIDE 150 mg/1 mL

VALCOR®

VALCOR® (doramectin and levamisole injection)
(5 mg/mL doramectin, 150 mg/mL levamisole hydrochloride)

CAUTION

Federal law restricts this drug to use by or on the order of a licensed veterinarian.

DESCRIPTION

VALCOR® injection is a ready-to-use, colorless to pale yellow, sterile solution containing 0.5% w/v doramectin and 15% w/v levamisole hydrochloride, for subcutaneous administration at a dose rate of 1 mL/25 kg of body weight to deliver a dose of 0.2 mg of doramectin and 6 mg of levamisole hydrochloride per kg of body weight. Each mL of VALCOR® contains 150 mg levamisole hydrochloride, 5 mg doramectin, 20 mg benzyl alcohol, 2.5 mg meglumine, 0.1 mg butylated hydroxyanisole (BHA), 0.1 mg butylated hydroxytoluene (BHT), and glycerol formal q.s.

INDICATIONS

VALCOR® is indicated for the treatment and control of the following species of parasites in beef cattle two months of age and older and in replacement dairy heifers less than 20 months of age. Not for use in beef bulls intended for breeding over 1 year of age, dairy calves, and veal calves.

Gastrointestinal Roundworms
(adults and fourth stage larvae)
Ostertagia ostertagi (including inhibited larvae)
O. lyrata
Haemonchus placei
Trichostrongylus axei
T. colubriformis
T. longispicularis*
Cooperia oncophora
C. pectinata*
C. punctata
C. surnabada
Bunostomum phlebotomum*
Strongyloides papillosus*
Oesophagostomum radiatum
Trichuris spp.*
Nematodirus helvetianus*

Lungworms
(adults and fourth stage larvae)
Dictyocaulus viviparus

Eyeworms (adults)
Thelazia spp.

Grubs (parasitic stages)
Hypoderma bovis
H. lineatum

Sucking Lice
Haematopinus eurysternus
Linognathus vituli
Solenopotes capillatus

Mange Mites
Psoroptes bovis
Sarcoptes scabiei

*Adults only

DOSAGE AND ADMINISTRATION

Inject subcutaneously in the neck as a single dose at a dosage of 0.2 mg doramectin (0.091 mg/lb) and 6 mg of levamisole hydrochloride per kg (2.72 mg/lb) of body weight. Each mL of VALCOR® contains 5 mg doramectin and 150 mg of levamisole hydrochloride which is sufficient to treat 55 lb (25 kg) of body weight. Do not inject more than 10 mL per injection site. Do not underdose. Ensure each animal receives a complete dose based on a current body weight. Underdosing may result in ineffective treatment and encourage the development of parasite resistance.
Use this product within 45 days of the first puncture. Puncture the 100 mL vial a maximum of 6 times and the 250 mL and 500 mL vials a maximum of 28 times, using a luer-lock syringe and needle no larger than 18 gauge. If anticipated to exceed maximum number of punctures, the use of automatic injection equipment or a repeater syringe is recommended. When using a draw-off spike or needle with bore diameter larger than 18 gauge, discard any product remaining in the vial immediately after use.

Body Weight, lb | Dose Volume, mL
110 | 2
220 | 4
330 | 6
440 | 8
550 | 10
660 | 12
770 | 14
880 | 16
990 | 18
1100 | 20
1210 | 22

WARNINGS AND PRECAUTIONS

WITHDRAWAL PERIODS AND RESIDUE WARNINGS:
Cattle must not be slaughtered for human consumption within 15 days following last treatment with this drug product. Not for use in female dairy cattle 20 months of age or older, including dry dairy cows; use in these cattle may cause drug residues in milk and/or in calves born to these cows or heifers. Not for use in beef calves less than 2 months of age, dairy calves, and veal calves. A withdrawal period has not been established for this product in pre-ruminating calves.

User Safety Warnings:
Not for human use. Keep out of reach of children. If accidental eye contact occurs, flush eyes immediately with water for 15 minutes and seek medical attention. If wearing contact lenses, flush eyes immediately with water before removing lenses then continue rinsing for at least 15 minutes. Do not eat, drink or smoke while handling the product. Wash hands after use. Take care to avoid accidental self-injection. If accidental injection occurs, seek medical attention and provide product package insert to medical professional. To obtain a Safety Data Sheet(s), contact Zoetis Inc. at 1-888-963-8471 or www.zoetis.com.
Animal Safety Warnings and Precautions:
Use of levamisole in cattle treated in the last few days with cholinesterase inhibitors such as organophosphates or with morantel may enhance the toxic effects of levamisole. Use together with caution.
Destruction of Hypoderma larvae (cattle grubs) at the period when these grubs are in vital areas may cause undesirable hostparasite reactions including the possibility of fatalities. Killing H. lineatum when it is in the tissue surrounding the gullet may cause bloat; killing H. bovis when it is in the vertebral canal may cause staggering or paralysis. These reactions are not specific to treatment with VALCOR™ and can occur with any successful treatment of grubs. Cattle should be treated either before or after these stages of grub development. Consult your veterinarian concerning the proper time for treatment. Follow recommended dosage carefully.
Reproductive safety has not been evaluated in bulls intended for breeding.
Environmental Warnings:
Studies indicate that when doramectin comes in contact with the soil, it readily and tightly binds to the soil and becomes inactive over time. Free doramectin may adversely affect fish and certain aquatic organisms. Do not permit water runoff from feedlots to enter streams or ponds. Do not contaminate water by direct application or by the improper disposal of drug containers. Dispose of containers in an approved landfill or by incineration.
As with other avermectins, doramectin is excreted in the dung of treated animals and can inhibit the reproduction and growth of pest and beneficial insects that use dung as a source of food and for reproduction. The magnitude and duration of such effects are species and life-cycle specific. When used according to label directions, the product is not expected to have an adverse impact on populations of dung-dependent insects.
Other Warnings:
Parasite resistance may develop to any dewormer and has been reported for most classes of dewormers. Treatment with a dewormer used in conjunction with parasite management practices appropriate to the geographic area and the animal(s) to be treated may slow the development of parasite resistance. Fecal examinations or other diagnostic tests and parasite management history should be used to determine if the product is appropriate for the herd, prior to the use of any dewormer. Following the use of any dewormer, effectiveness of treatment should be monitored (for example, with the use of a fecal egg count reduction test or another appropriate method). A decrease in a drug’s effectiveness over time as calculated by fecal egg count reduction tests may indicate the development of resistance to the dewormer administered. Your parasite management plan should be adjusted accordingly based on regular monitoring.

ADVERSE REACTIONS

This product is likely to cause swelling at the injection site. Tissue damage at the injection site may also occur, including possible granulomas and necrosis. These reactions have resolved without treatment. Local tissue reaction may result in trim loss of edible tissue at slaughter. A single death attributed to clostridial infection associated with the injection of VALCOR® was reported in a non-pivotal effectiveness study. Observe cattle for injection site reactions. If injection site reactions are suspected, consult your veterinarian. This product is not for intravenous or intramuscular use. Hypersalivation may be observed; however, this reaction will disappear within a few hours. If this condition persists, a veterinarian should be consulted.

Contact Information:
Contact Zoetis Inc. at 1-888-963-8471 or www.zoetis.com. To report suspected adverse drug experiences, contact Zoetis Inc. at 1-888-963-8471. For additional information about reporting adverse drug experiences for animal drugs, contact FDA at 1-888-FDA-VETS or http://www.fda.gov/reportanimalae.

EFFECTIVENESS

The effectiveness of VALCOR® against gastrointestinal nematodes and ectoparasites was demonstrated in five dose confirmation studies and a multi-site field study and is described below. VALCOR®-treated cattle (N = 373) had either naturally or artificially acquired infections or infestations originating from a wide range of geographical settings. These studies demonstrate that VALCOR® is effective against a variety of internal and external parasites. Across three dose confirmation studies and a multi-site field study, the VALCOR®-treated animals had a fecal egg count reduction between 99.9% and 100% when the pre-treatment and post-treatment arithmetic means of fecal egg counts were compared.
a. Multi-site Study
A multi-site study was conducted to evaluate the effectiveness of VALCOR® against naturally acquired gastrointestinal nematodes in a field setting. In this six-site study, 425 cattle (steers, heifers, pregnant heifers, pregnant cows and late lactation cows) were enrolled and randomized to one of two treatment groups: saline, N = 106, (0.04 mL/kg); VALCOR®, N = 319, (0.2 mg/kg doramectin; 6 mg/kg, levamisole hydrochloride (HCl). Effectiveness of VALCOR® was achieved with >99% reduction in fecal egg counts compared to the saline-treated group on Day 14. Percent efficacy, by site, ranged from 99.4% to 100.0% on Day 14.
b. Dose Confirmation Studies
Artificial Nematodirus helvetianus Challenge Study
A study was conducted to evaluate the effectiveness of VALCOR® against cattle infected with an artificial N. helvetianus challenge. In this study, 24 artificially infected cattle (9-week old Holstein steers) were enrolled and randomized to one of three treatment groups: saline group, N = 8, (0.04 mL/kg); DECTOMAX®, N = 8, (0.2 mg/kg doramectin); VALCOR®, N = 8, (0.2 mg/kg doramectin; 6 mg/kg, levamisole HCl). Effectiveness of VALCOR® was achieved with 100% efficacy against adult N. helvetianus compared to the saline-treated group with 0% efficacy and the DECTOMAX®-treated group with 4.9% efficacy on Day 14.
Nematodirus helvetianus and Cooperia oncophora Natural Infection Studies
A study was conducted to evaluate the effectiveness of VALCOR® against cattle naturally infected with N. helvetianus and C. oncophora. In this study, 36 naturally infected cattle (4-10 month old, male and female beef and dairy crossbred) were enrolled and randomized to one of three treatment groups: saline, N = 12, (0.04 mL/kg); DECTOMAX®, N = 12, (0.2 mg/kg doramectin); VALCOR™, N = 12, (0.2 mg/kg doramectin; 6 mg/kg, levamisole HCl). Effectiveness of VALCOR® was achieved with 100% efficacy against adult N. helvetianus and 100% efficacy against C. oncophora compared to the saline-treated group with 0% efficacy and the DECTOMAX® group with 87.9% and 99.4% efficacy against N. helvetianus and C. oncophora, respectively, on Day 14.
A second study was conducted to evaluate the effectiveness of VALCOR® against cattle naturally infected with N. helvetianus and C. oncophora. In this study, 30 naturally infected cattle (7-month old, male and female beef crossbred) were enrolled and randomized to one of three treatment groups: saline, N = 10, (0.04 mL/kg); DECTOMAX®, N = 10, (0.2 mg/kg doramectin); VALCOR®, N = 10, (0.2 mg/kg doramectin; 6 mg/kg, levamisole HCl). Effectiveness of VALCOR™ was achieved with 99.1% efficacy against adult N. helvetianus and 99.7% efficacy against C. oncophora compared to the saline-treated group with 0% efficacy and DECTOMAX® group with 25.4% and 49.3% efficacy, against N. helvetianus and C. oncophora, respectively, on Day 14.
Sucking Lice Natural Infestation Studies
A study was conducted to evaluate the effectiveness of VALCOR® against cattle naturally infested with sucking lice (Linognathus vituli, Haematopinus eurysternus, and Solenopotes capillatus). In this study, 24 naturally infested cattle (beef and dairy breed females and castrate males) were enrolled and randomized to one of two groups: sterile water group, N = 12 (0.04 mL/kg) and VALCOR™, N = 12, (0.2 mg/kg doramectin; 6 mg/kg, levamisole HCl). Effectiveness of VALCOR® was achieved with 99.9% efficacy against immature and adult sucking lice up to 56 days after treatment.
A second study was conducted to evaluate the effectiveness of VALCOR® against cattle naturally infested with sucking lice (L. vituli). In this study, 24 naturally infested cattle (beef and dairy breed females and castrate males) were enrolled and randomized to one of two groups: saline group, N = 12 (0.04 mL/kg) and VALCOR®, N = 12, (0.2 mg/kg doramectin; 6 mg/kg, levamisole HCl). Effectiveness of VALCOR® was achieved with 99.4% efficacy against immature and adult sucking lice up to 56 days after treatment

TARGET ANIMAL SAFETY

Margin of Safety: Subcutaneous administration of VALCOR® was well tolerated in calves as young as 3 months of age at 1, 2, or 3 times the recommended dose. Dose-dependent post-dose hypersalivation was seen in all treated groups compared to the controls. All cases of hypersalivation were mild, transient, and resolved without further medical intervention. Dose-related injection site reactions were observed, and those in the 1X group resolved between 21 and 28 days post injection. Injection site reactions were primarily swelling which resolved between 21 and 28 days post injection. Findings from the injection sites included swelling, edema, inflammation, muscle necrosis and fibrosis.
Female Reproductive Safety: The reproductive safety of VALCOR® was established in two studies with female cattle. First, a single dose of VALCOR® was administered subcutaneously at 3 times the recommended dose at times coinciding with folliculogenesis, implantation, or organogenesis, and had no effects on conception, calving, abortion, and stillbirth rates, and post-natal viability up to 30±2 days post-calving. There were no congenital abnormalities. The only test article-related change was an increase in incidence and duration of swelling at injection sites compared with control, but all swellings eventually resolved. In a second study, a single dose of VALCOR® administered subcutaneously at 3 times the recommended dose at either early or late gestation had no effects on calving, abortion, and stillbirth rates, and post-natal viability up to 30±2 days post-calving. One control calf and two treated calves were born with congenital abnormalities and did not survive. These were not determined to be test article-related. The only test article-related change was an increase in incidence and duration of swelling at injection sites, but all swellings eventually resolved. Not for use in bulls intended for breeding over 1 year of age, as reproductive safety has not been evaluated.

HOW SUPPLIED

VALCOR® is available in 100 mL, 250 mL and 500 mL multi-dose, rubber-capped glass vials.

STORAGE, HANDLING, AND DISPOSAL

Store below 25°C (77°F). Do not expose to light for extended periods of time. Do not contaminate water by direct application or by improper disposal of drug containers. Dispose of containers in an approved landfill or by incineration.

Approved by FDA under NADA # 141-553

zoetis
Distributed by:
Zoetis Inc.
Kalamazoo, MI 49007
February 2025
40052208

PRINCIPAL DISPLAY PANEL - 100 mL Label

40052152

PRINCIPAL DISPLAY PANEL - 250 mL Label

40052207

PRINCIPAL DISPLAY PANEL - 500 mL Label

40052211